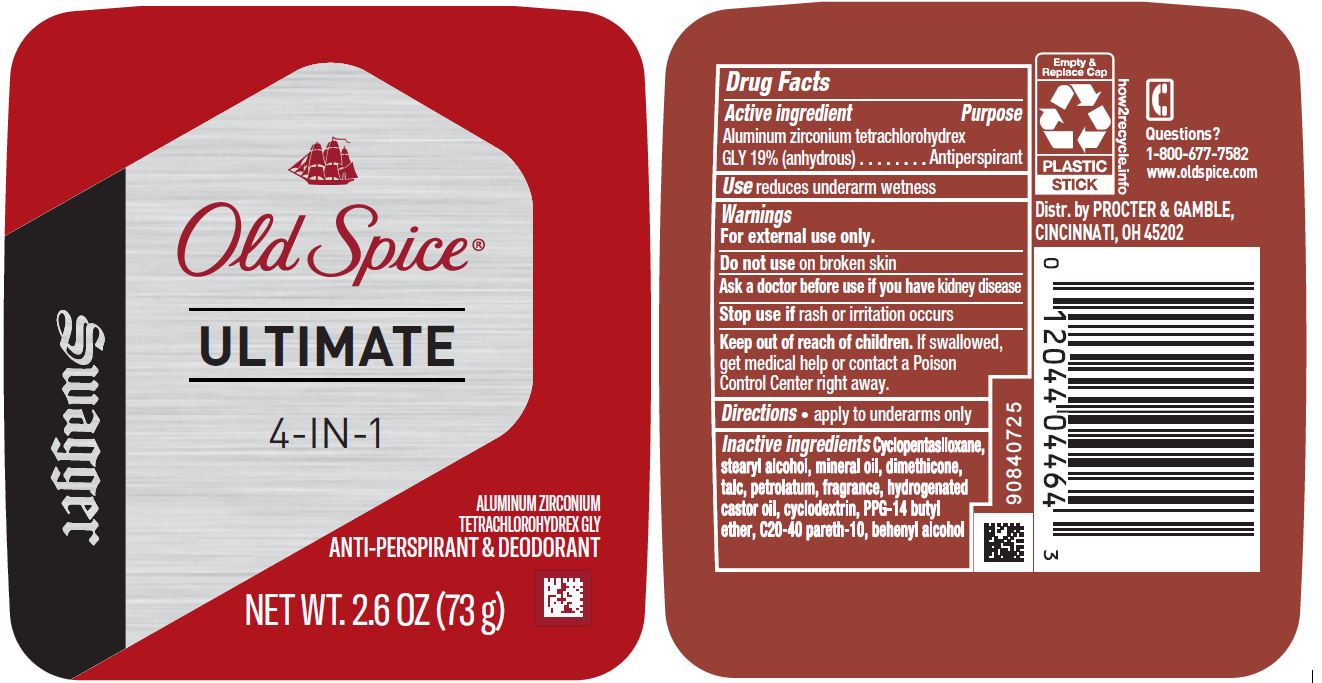 DRUG LABEL: Old Spice Ultimate 4in1 Swagger
NDC: 69423-472 | Form: STICK
Manufacturer: The Procter & Gamble Manufacturing Company
Category: otc | Type: HUMAN OTC DRUG LABEL
Date: 20200605

ACTIVE INGREDIENTS: ALUMINUM ZIRCONIUM TETRACHLOROHYDREX GLY 19 g/100 g
INACTIVE INGREDIENTS: BETADEX; CYCLOMETHICONE 5; STEARYL ALCOHOL; MINERAL OIL; DIMETHICONE; TALC; HYDROGENATED CASTOR OIL; PPG-14 BUTYL ETHER; C20-40 PARETH-10; DOCOSANOL; PETROLATUM

Old Spice® Ultimate 4-in-1 Swagger™

Drug Facts

Active ingredient

Aluminum zirconium tetrachlorohydrex Gly 19% (anhydrous)

Purpose

Antiperspirant

Use

reduces underarm wetness

Warnings

For external use only.

Do not use on broken skin

Ask a doctor before use if you have kidney disease

Stop use if rash or irritation occurs

Keep out of reach of children.
If swallowed, get medical help or contact a Poison Control Center right away.

Directions

- apply to underarms only

Inactive ingredients

cyclopentasiloxane, stearyl alcohol, mineral oil, dimethicone, talc, petrolatum, fragrance, hydrogenated castor oil, cyclodextrin, PPG-14 butyl ether, C20-40 pareth-10, behenyl alcohol

Questions?

1-800-677-7582

Dist. by PROCTER & GAMBLE,
CINCINNATI, OH 45202.

PRINCIPAL DISPLAY PANEL - 73 g Cylinder Label

Old Spice®

ULTIMATE

4-IN-1

SWAGGER

ALUMINUM ZIRCONIUM

TETRACHLOROHYDREX GLY

ANTI-PERSPIRANT & DEODORANT

NET WT. 2.6 OZ (73 g)